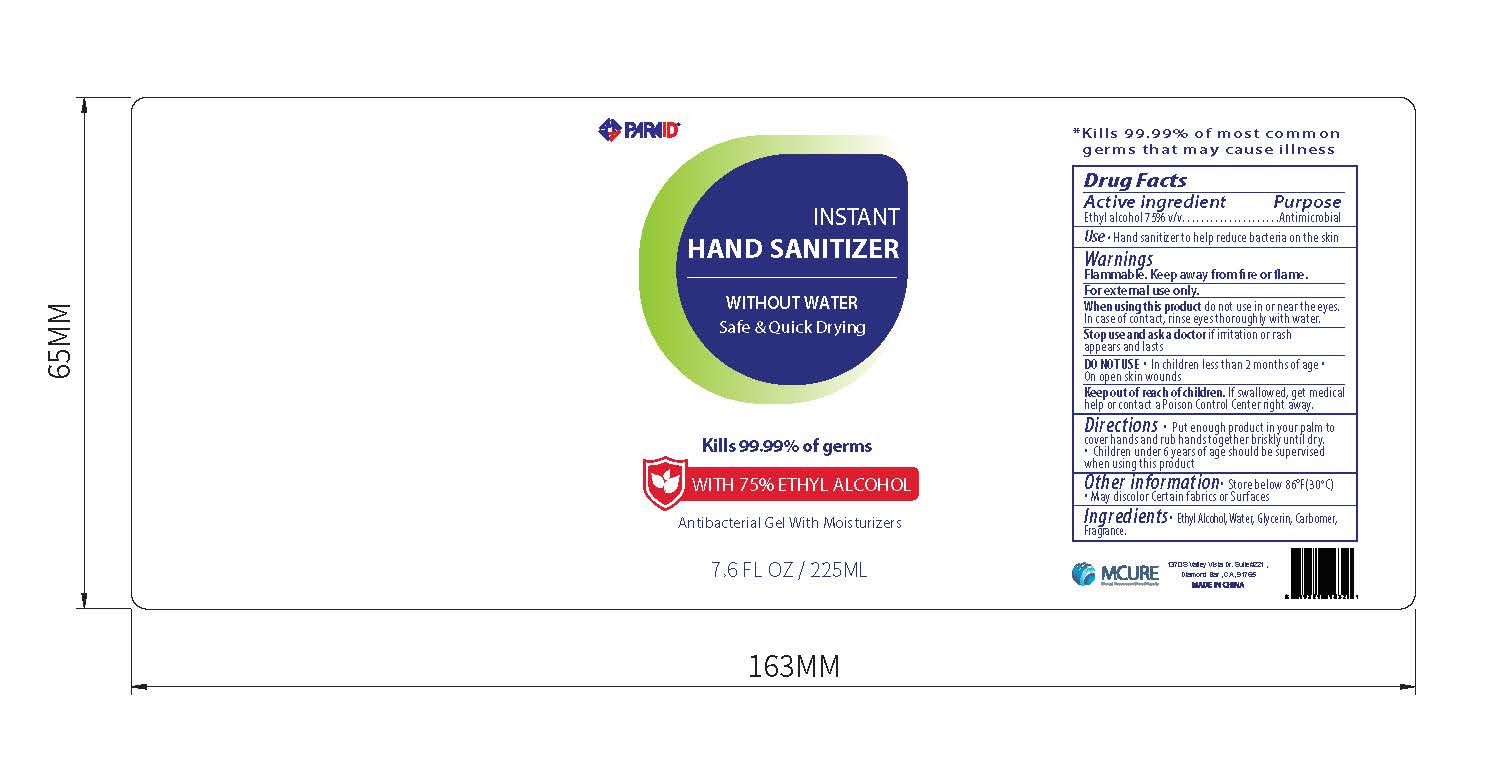 DRUG LABEL: 7.6OZ Hand Sanitizer
NDC: 52486-260 | Form: GEL
Manufacturer: MCURE HEALTH SOLUTIONS INC.
Category: otc | Type: HUMAN OTC DRUG LABEL
Date: 20200401

ACTIVE INGREDIENTS: ALCOHOL 75 mL/100 mL
INACTIVE INGREDIENTS: CARBOXYPOLYMETHYLENE; GLYCERIN 1.45 mL/100 mL; WATER

Active Ingredient(s)

Ethyl Alcohol 75% v/v. Purpose: Antiseptic

Purpose

Antiseptic, Hand Sanitizer

Use

Hand Sanitizer to help reduce bacteria that potentially can cause disease. For use when soap and water are not available.

Warnings

For external use only. Flammable. Keep away from heat or flame

Do not use

- in children less than 2 months of age
- on open skin wounds

When using this product do not use in or near the eyes.

In case of contact, rinse eyes thoroughly with water.

Stop use and ask a doctor if irritation or rash occurs. These may be signs of a serious condition.

Keep out of reach of children. If swallowed, get medical help or contact a Poison Control Center right away.

Directions

- Place enough product on hands to cover all surfaces. Rub hands together until dry.
- Supervise children under 6 years of age when using this product to avoid swallowing.

Other information

- Store below 30°C (86°F)

Inactive ingredients

Glycerin, Water, Carbomer, Fragrance

Package Label - Principal Display Panel

225 ml NDC: 52486-260-03